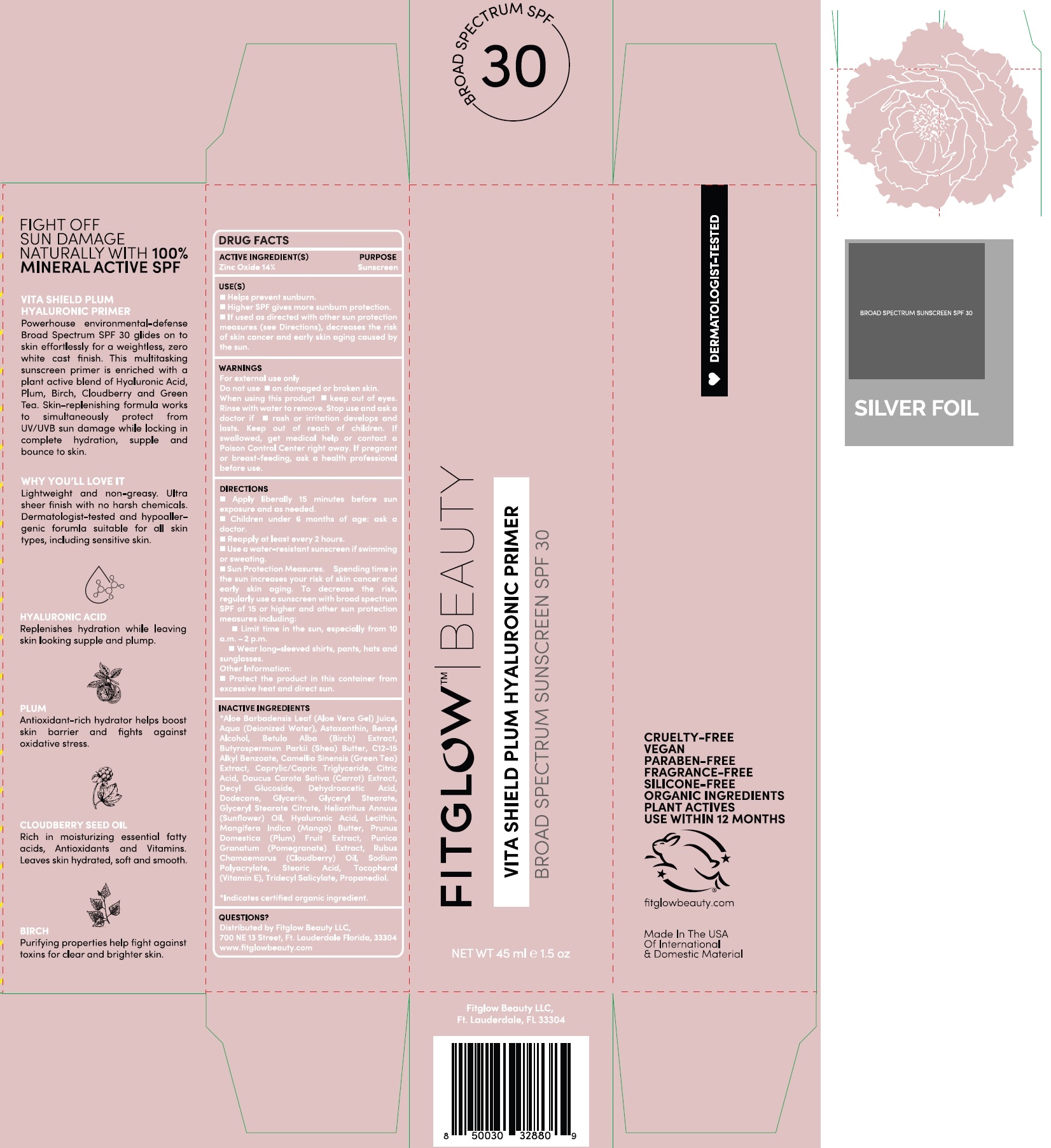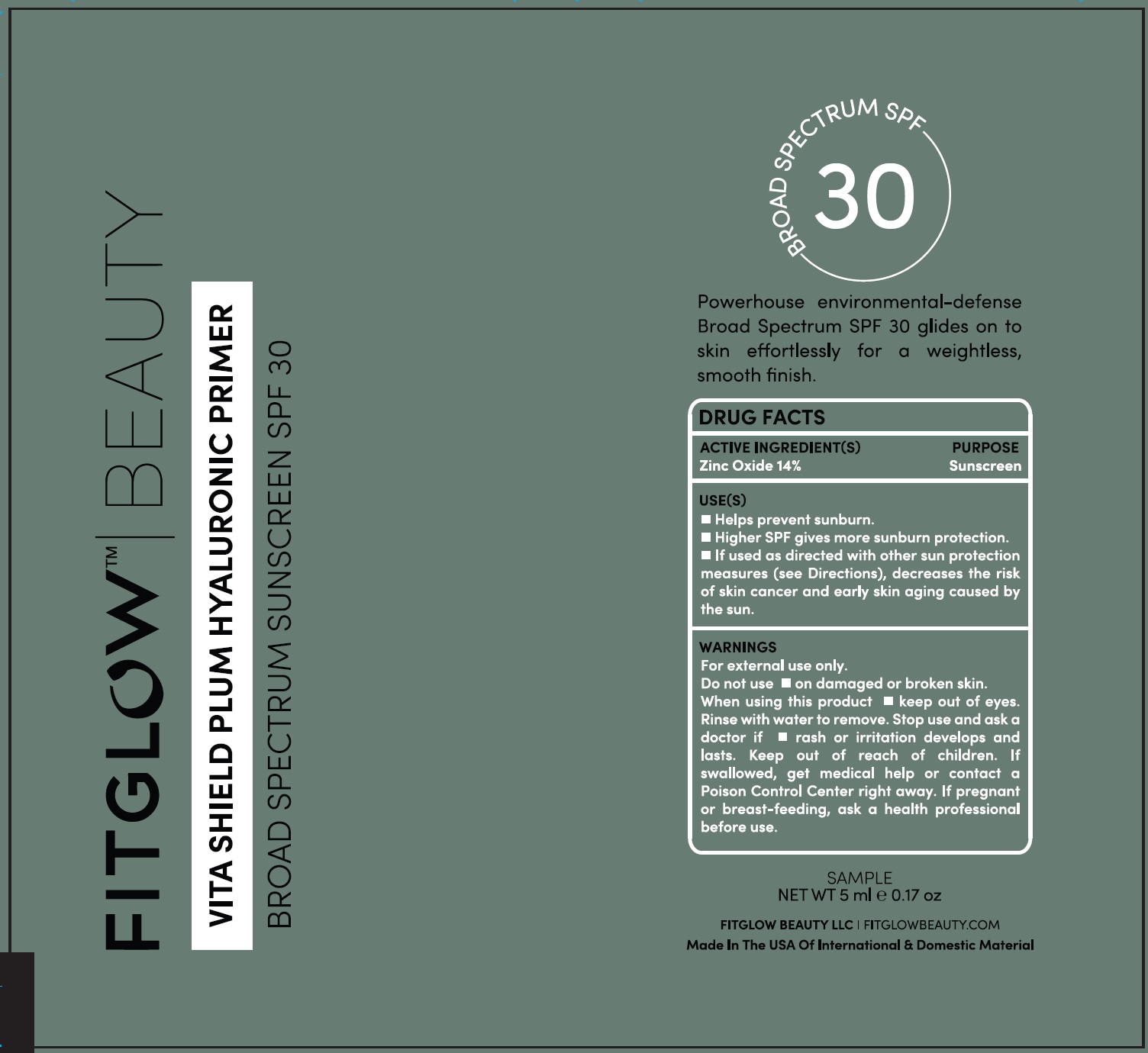 DRUG LABEL: FITGLOW Vita Shield Hyaluronic Primer SPF-30
NDC: 72975-277 | Form: CREAM
Manufacturer: FITGLOW BEAUTY LLC
Category: otc | Type: HUMAN OTC DRUG LABEL
Date: 20231111

ACTIVE INGREDIENTS: ZINC OXIDE 140 mg/1 mL
INACTIVE INGREDIENTS: ALOE VERA LEAF; WATER; ASTAXANTHIN; BENZYL ALCOHOL; SHEA BUTTER; ALKYL (C12-15) BENZOATE; GREEN TEA LEAF; MEDIUM-CHAIN TRIGLYCERIDES; CITRIC ACID MONOHYDRATE; CARROT; DECYL GLUCOSIDE; DEHYDROACETIC ACID; DODECANE; GLYCERIN; GLYCERYL MONOSTEARATE; GLYCERYL STEARATE CITRATE; HELIANTHUS ANNUUS FLOWERING TOP; HYALURONIC ACID; MANGO; PLUM; PUNICA GRANATUM ROOT BARK; STEARIC ACID; TOCOPHEROL; TRIDECYL SALICYLATE; PROPANEDIOL

FITGLOW Vita Shield Hyaluronic Primer SPF-30

ACTIVE INGREDIENT(S)

Zinc Oxide 14%

PURPOSE

Sunscreen

USE(S)

- Helps prevent sunburn.
- Higher SPF gives more sunburn protection.
- If used as directed with other sun protection measures (see Directions), decreases the risk of skin cancer and early skin aging caused by the sun.

WARNINGS

For external use only

Do not use

- on damaged or broken skin.

When using this product

- keep out of eyes. Rinse with water to remove.

Stop use and ask a doctor if

- rash or irritation develops and lasts.

Keep out of reach of children.

If swallowed, get medical help or contact a Poison Control Center right away.

If pregnant or breast-feeding,

ask a health professional before use.

DIRECTIONS

- Apply liberally 15 minutes before sun exposure and as needed.
- Children under 6 months of age: ask a doctor.
- Reapply at least every 2 hours.
- Use a water-resistant sunscreen if swimming or sweating.
- Spending time in the sun increases your risk of skin cancer and early skin aging. To decrease the risk, regularly use a sunscreen with broad spectrum SPF of 15 or higher and other sun protection measures including: Sun Protection Measures.
- Limit time in the sun, especially from 10 a.m.-2 p.m.
- Wear long-sleeved shirts, pants, hats and sunglasses.

Other Information:

- Protect the product in this container from excessive heat and direct sun.

INACTIVE INGREDIENTS

*Aloe Barbadensis Leaf (Aloe Vera Gel) Juice, Aqua (Deionized Water), Astaxanthin, Benzyl Alcohol, Betula Alba (Birch) Extract, Butyrospermum Parkii (Shea) Butter,C12-15 Alkyl Benzoate, Camellia Sinensis (Green Tea) Extract, Caprylic/Capric Triglyceride, Citric Acid, Daucus Carota Sativa (Carrot) Extract, Decyl Glucoside, Dehydroacetic Acid, Dodecane, Glycerin, Glyceryl Stearate, Glyceryl Stearate Citrate, Helianthus Annuus (Sunflower) Oil, Hyaluronic Acid, Lecithin, Mangifera Indica (Mango) Butter, Prunus Domestica (Plum) Fruit Extract, Punica Granatum (Pomegranate) Extract, Rubus Chamaemorus (Cloudberry) Oil, Sodium Polyacrylate, Stearic Acid, Tocopherol (Vitamin E), Tridecyl Salicylate, Propanediol.

*Indicates certified organic ingredient.

QUESTIONS?

Distributed by Fitglow Beauty LLC, 700 NE 13 Street, Ft. Lauderdale Florida, 33304 www.fitglowbeauty.com